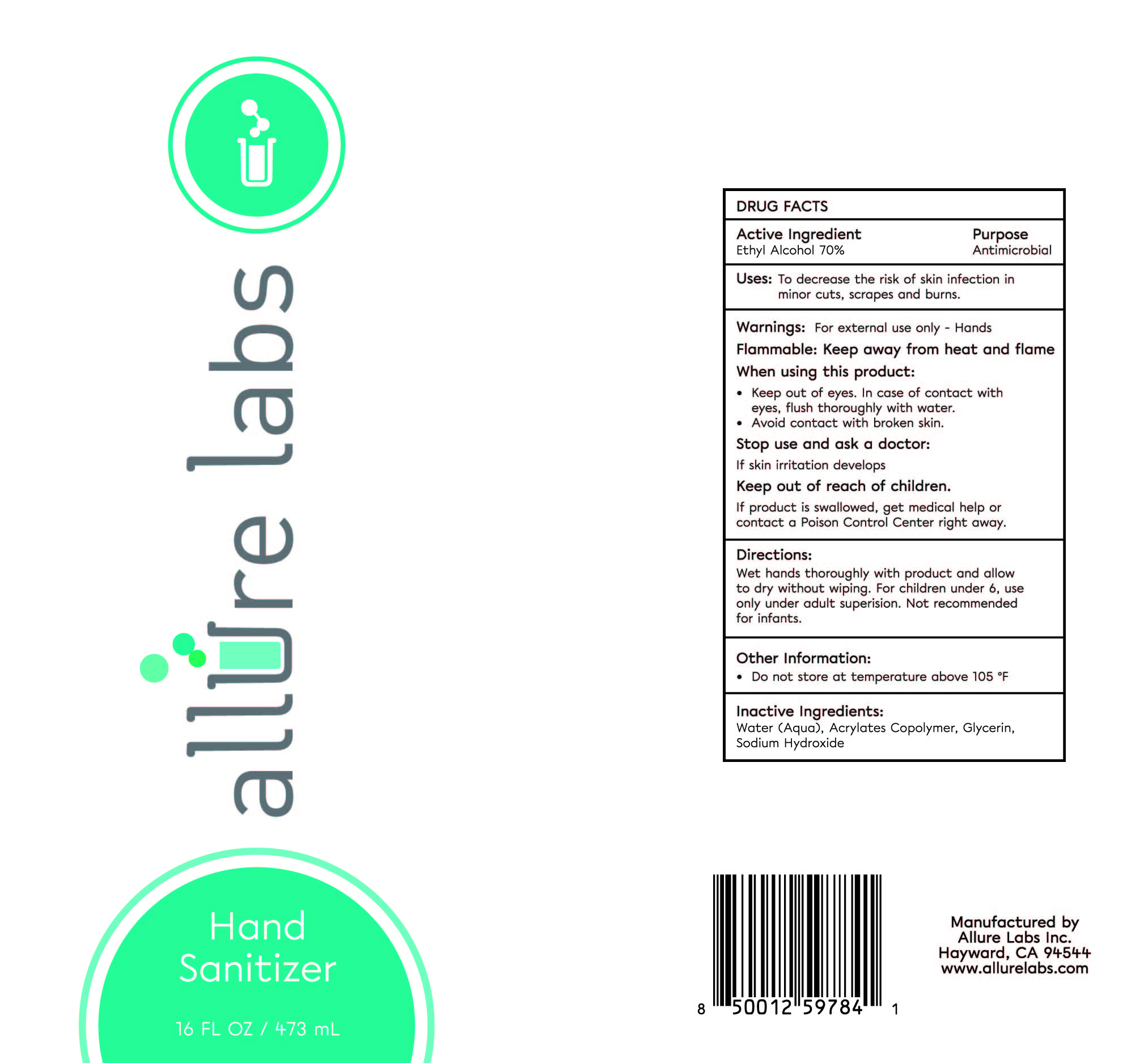 DRUG LABEL: Hand Sanitizer
NDC: 62742-4185 | Form: GEL
Manufacturer: Allure Labs Inc
Category: otc | Type: HUMAN OTC DRUG LABEL
Date: 20200330

ACTIVE INGREDIENTS: ALCOHOL 700 mg/1 mL
INACTIVE INGREDIENTS: WATER; GLYCERIN; CARBOMER 940; TROLAMINE; BENZYL BENZOATE; CITRAL; GERANIOL; .ALPHA.-HEXYLCINNAMALDEHYDE; LIMONENE, (+)-; LINALOOL, (+/-)-

DRUG FACTS

Active Ingredients:

Ethyl Alcohol - 70%

Purpose: Antimicrobial

INDICATIONS AND USAGE

Uses: To decrease the risk of skin infection in minor cuts, scrapes and burns.

WARNINGS

Warning: For External use only - Hands

Flammable: Keep away from heat and Flame

When using this products:

- Keep out of eyes. In case of contact with eyes, flush thoroughly with water.

Stop use and ask a doctor if skin irritation develops.

Keep out of reach of children:

- If product is swallowed, get medical help or contact a Poison Control Center right away.

Directions:

- Wet hands throughly with product and allow to dry without wiping. For children under 6, use only under adult supervision. Not recommended for infants.

INACTIVE INGREDIENT

Inactive Ingredients: Water (Aqua), Glycerin, Acrylate Copolymer, Sodium Hydroxide

PACKAGE LABEL

Manufactured By

Allure Labs, Inc.

Hayward, CA 94544

www.allurelabs.com